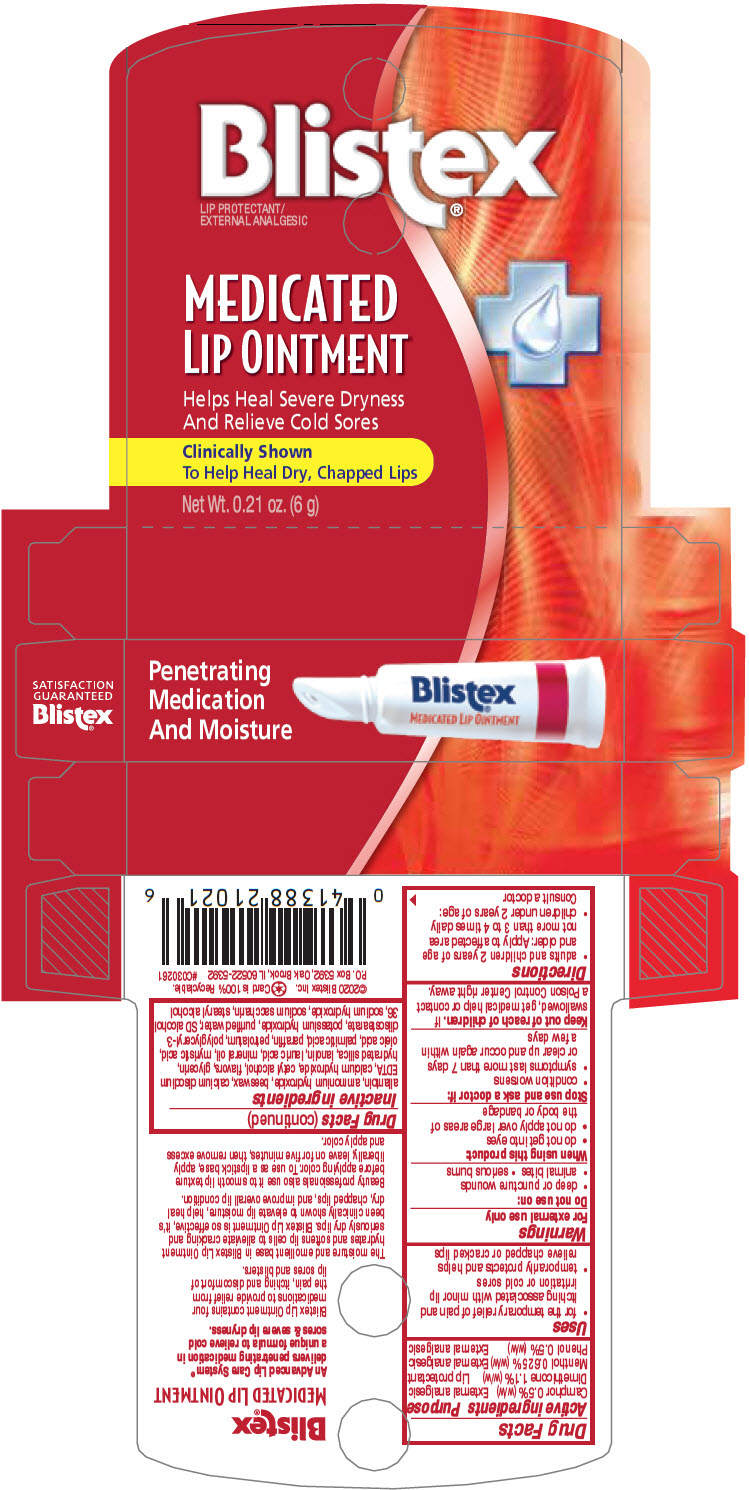 DRUG LABEL: Blistex 
NDC: 10157-9951 | Form: OINTMENT
Manufacturer: Blistex Inc.
Category: otc | Type: HUMAN OTC DRUG LABEL
Date: 20241211

ACTIVE INGREDIENTS: Dimethicone 1.1 g/100 g; Camphor (synthetic) 0.5 g/100 g; Menthol, unspecified form 0.625 g/100 g; Phenol 0.5 g/100 g
INACTIVE INGREDIENTS: allantoin; ammonia; yellow wax; edetate calcium disodium anhydrous; calcium hydroxide; cetyl alcohol; glycerin; hydrated silica; lanolin; lauric acid; mineral oil; myristic acid; oleic acid; palmitic acid; paraffin; petrolatum; polyglyceryl-3 diisostearate; potassium hydroxide; water; sodium hydroxide; saccharin sodium; stearyl alcohol

Blistex®
Medicated Lip ointment

Drug Facts

ACTIVE INGREDIENT

Active ingredients | Purpose
Camphor 0.5% (w/w) | External analgesic
Dimethicone 1.1% (w/w) | Lip protectant
Menthol 0.625% (w/w) | External analgesic
Phenol 0.5% (w/w) | External analgesic

Uses

- for the temporary relief of pain and itching associated with minor lip irritation or cold sores
- temporarily protects and helps relieve chapped or cracked lips

Warnings

For external use only

Do not use on

- deep or puncture wounds
- animal bites
- serious burns

When using this product

- do not get into eyes
- do not apply over large areas of the body or bandage

Stop use and ask a doctor if

- condition worsens
- symptoms last more than 7 days or clear up and occur again within a few days

Keep out of reach of children. If swallowed, get medical help or contact a Poison Control Center right away.

Directions

- adults and children 2 years of age and older: Apply to affected area not more than 3 to 4 times daily
- children under 2 years of age: Consult a doctor

Inactive ingredients

allantoin, ammonium hydroxide, beeswax, calcium disodium EDTA, calcium hydroxide, cetyl alcohol, flavors, glycerin, hydrated silica, lanolin, lauric acid, mineral oil, myristic acid, oleic acid, palmitic acid, paraffin, petrolatum, polyglyceryl-3 diisostearate, potassium hydroxide, purified water, SD alcohol 36, sodium hydroxide, sodium saccharin, stearyl alcohol

PRINCIPAL DISPLAY PANEL - 6 g Tube Carton

Penetrating
Medication
And Moisture

Blistex®
MEDICATED LIP OINTMENT